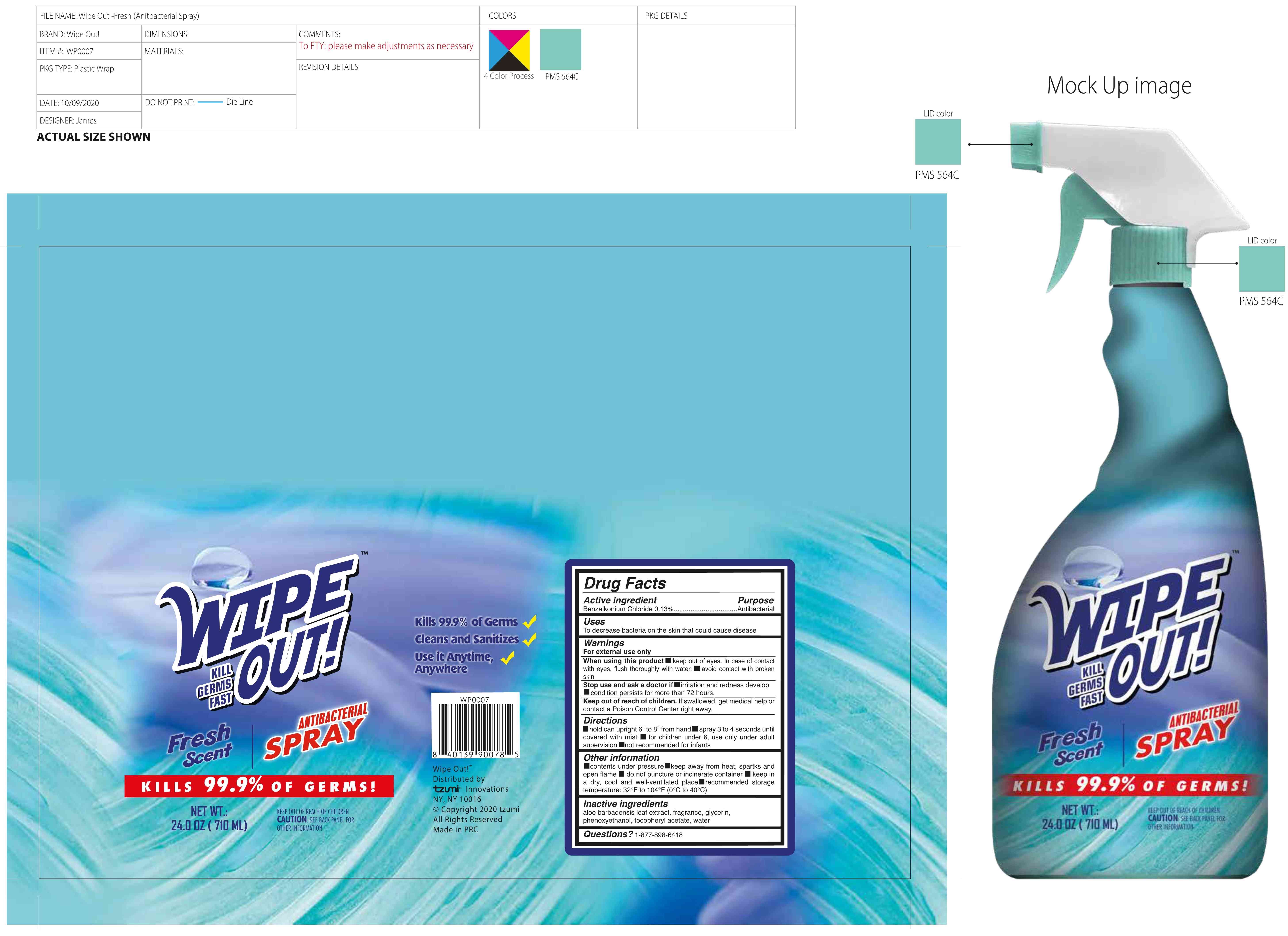 DRUG LABEL: Wipe Out-Fresh Scent
NDC: 75606-003 | Form: SPRAY
Manufacturer: Xiamen Tesimeier Biotechnology Co., Ltd.
Category: otc | Type: HUMAN OTC DRUG LABEL
Date: 20201017

ACTIVE INGREDIENTS: BENZALKONIUM CHLORIDE 0.13 g/100 mL
INACTIVE INGREDIENTS: ALOE VERA LEAF; FRAGRANCE CLEAN ORC0600327; PHENOXYETHANOL; GLYCERIN; .ALPHA.-TOCOPHEROL ACETATE; WATER

75606-003
Wipe Out Spray-Fresh Scent

Active Ingredient(s)

Benzalkonium Chloride 0.13%

Purpose

Antibacterial

Use

To decrease bacteria on the skin that could cause disease

Warnings

For external use only

When using this product keep out of eyes. In case of contact with eyes, flush thoroughly with water. avoid contact with broken skin

Stop use and ask a doctor if irritation and redness develop condition persists for more than 72 hours.

Keep out of reach of children. If swallowed, get medical help or contact a Poison Control Center right away.

Do not use

/

When using this product keep out of eyes. In case of contact with eyes, flush thoroughly with water. avoid contact with broken skin

Stop use and ask a doctor if irritation and redness develop condition persists for more than 72 hours.

Keep out of reach of children. If swallowed, get medical help or contact a Poison Control Center right away.

Stop use and ask a doctor if irritation and redness develop condition persists for more than 72 hours.

Keep out of reach of children. If swallowed, get medical help or contact a Poison Control Center right away.

Directions

hold can upright 6” to 8” from hand
spray 3 to 4 seconds until covered with mist
for children under 6, use only under adult supervision
not recommended for infants

Other information

contents under pressure
keep away from heat, spartks and open flame
do not puncture or incinerate container
keep in a dry, cool and well-ventilated place
recommended storage temperature: 32°F to 104°F (0℃ to 40℃)

Inactive ingredients

aloe barbadensis leaf extract, fragrance, glycerin, phenoxyethanol, tocopheryl acetate, water